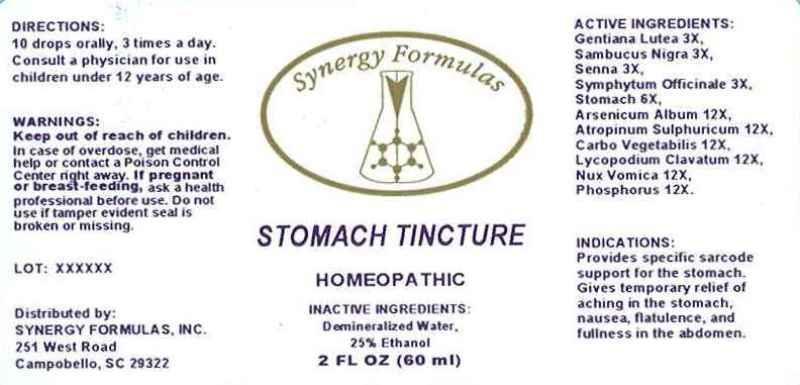 DRUG LABEL: Stomach Tincture
NDC: 43772-0001 | Form: LIQUID
Manufacturer: Synergy Formulas
Category: homeopathic | Type: HUMAN OTC DRUG LABEL
Date: 20120822

ACTIVE INGREDIENTS: GENTIANA LUTEA ROOT 3 [hp_X]/60 mL; SAMBUCUS NIGRA FLOWERING TOP 3 [hp_X]/60 mL; SENNA LEAF 3 [hp_X]/60 mL; TRIPE 6 [hp_X]/60 mL; ARSENIC TRIOXIDE 12 [hp_X]/60 mL; ATROPINE SULFATE 12 [hp_X]/60 mL; ACTIVATED CHARCOAL 12 [hp_X]/60 mL; LYCOPODIUM CLAVATUM SPORE 12 [hp_X]/60 mL; STRYCHNOS NUX-VOMICA SEED 12 [hp_X]/60 mL; PHOSPHORUS 12 [hp_X]/60 mL
INACTIVE INGREDIENTS: WATER; ALCOHOL

Stomach Tincture

ACTIVE INGREDIENTS:

Gentiana Lutea 3X,

Sanbucus Nigra 3X,

Senna 3X,

Symphytum Officinale 3X,

Stomach 6X,

Arsenicum Album 12X,

Atropinum Sulphuricum 12X,

Carbo Vegetabilis 12X,

Lycopodium Clavatum 12X,

Nux Vomica 12X,

Phosphorus 12X.

PURPOSE

INDICATIONS:

Provides specific sarcode support for the stomach. Gives temporary relilef of aching in the stomach, nausea, flatulence, and fullness in the abdomen.

WARNINGS:

Keep out of reach of children. Incase of overdose, get medical help or contact a Posion Control Center right away. If pregnant or breast-feeding, ask a health professional before use. Do not use if tamper evident seal is broken or missing.

DIRECTIONS:

10 drops orally, 3 times a day. Consult a physician for use in children under 12 years of age.

INACTIVE INGREDIENT:

Demineralized Water.

25% Ethanol

Keep out of reach of children. Incase of overdose, get medical help or contact a Posion Control Center right away.

INDICATIONS:

Provides specific sarcode support for the stomach. Gives temporary relilef of aching in the stomach, nausea, flatulence, and fullness in the abdomen.

QUESTIONS

Distributed by:

SYNERGY FORMULAS, INC.

251 West Road

Campobello, SC 29322

PACKAGE LABEL

Synergy Formulas

STOMACH TINCTURE

HOMEOPATHIC

2 FL oz (60 ml)